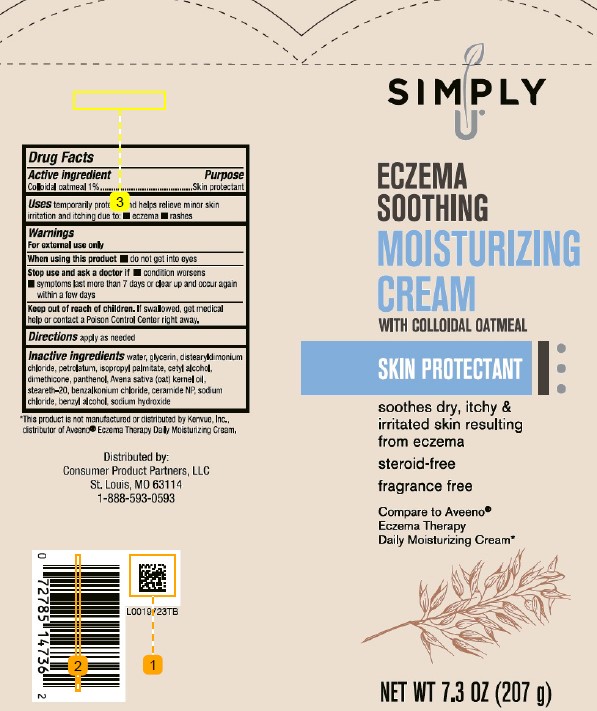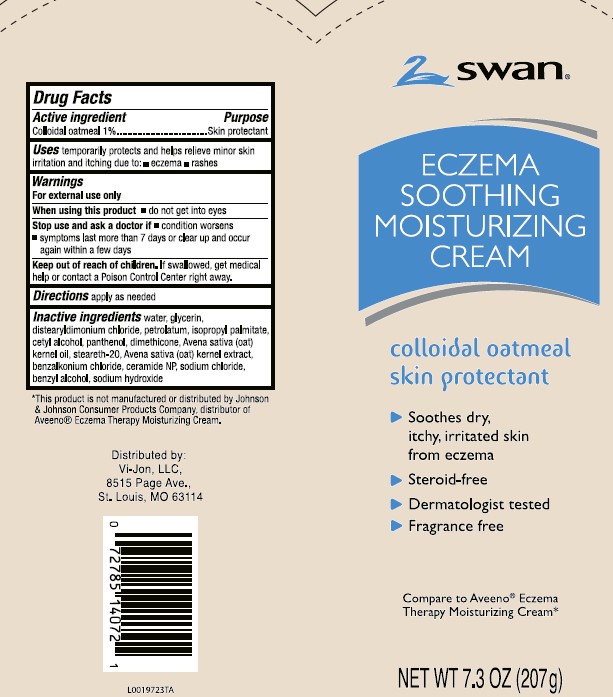 DRUG LABEL: Eczema Soothing Moisturizing Cream
NDC: 11344-965 | Form: CREAM
Manufacturer: Consumer Product Partners, LLC
Category: otc | Type: HUMAN OTC DRUG LABEL
Date: 20250507

ACTIVE INGREDIENTS: OATMEAL 10 mg/1 g
INACTIVE INGREDIENTS: WATER; GLYCERIN; DISTEARYLDIMONIUM CHLORIDE; PETROLATUM; ISOPROPYL PALMITATE; CETYL ALCOHOL; DIMETHICONE; PANTHENOL; OAT KERNEL OIL; STEARETH-20; BENZALKONIUM CHLORIDE; CERAMIDE 3; SODIUM CHLORIDE; BENZYL ALCOHOL; SODIUM HYDROXIDE

Swan_Simply U 965.001/965AC
Eczema Soothing Moisturizing Cream

Active ingredient

Colloidal oatmeal 1%

Purpose

Skin protectant

Uses

temporarily protects and helps relieve minor skin irritation and itching due to:

- eczema
- rashes

Warnings

For external use only

When using this product

- do not get into eyes

Stop use and ask a doctor if

- condition worsens
- symptoms last more than 7 days or clear up and occur again withing a few days

Keep out of reach of children.

If swallowed, get medical help or contact a Poison Control Center right away.

Directions

apply as needed

Inactive ingredients

water, glycerin, distearyldimonium chloride, petrolatum, isopropyl palmitate, cetyl alcohol, dimethicone, panthenol, Avena sativa (oat) kernel oil, steareth-20, benzalkonium chloride, ceramide NP, sodium chloride, benzyl alcohol, sodium hydroxide

Disclaimer

*This product is not manufactured or distributed by Kenvue, Inc., distributor of Aveeno® Eczema Therapy Daily Moisturizing Cream.

Adverse reaction

Distributed by:

Consumer Product Partners, LLC

St. Louis, MO 63114

1-888-593-0593

Principal panel display

Swan®

ECZEMA SOOTHING MOISTURIZING CREAM

colloidal oatmeal

skin protectant

- Sooths dry skin, itchy, irritated skin from eczema
- Steroid-free
- Dermatologist tested
- Fragrance free

Compare to Aveeno® Eczema Therapy Moisturizing Cream*

NET WT 7.3 OZ (207 g)

Principal panel display

SIMPLY U®

ECZEMA SOOTHING

MOISTURIZING CREAM

WITH COLLOIDAL OATMEAL

SKIN PROTECTANT

soothes dry, ichy, & irriated skin resulting from eczema

steroid-free

fragrance free

Compare to Aveeno®Eczema Therapy Daily Moisturizing Cream*

NET WT 7.3 OZ (207 g)